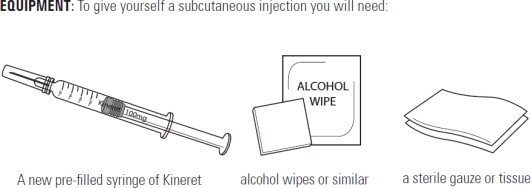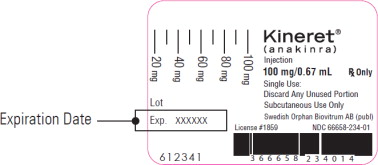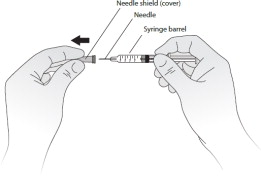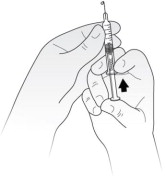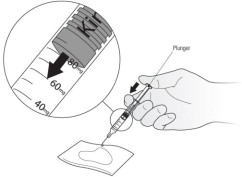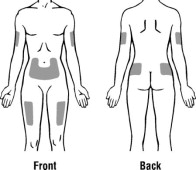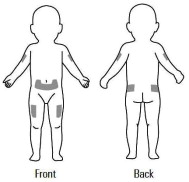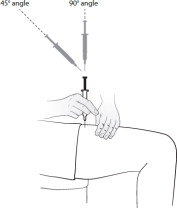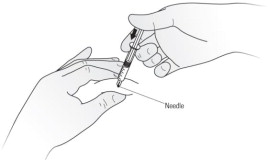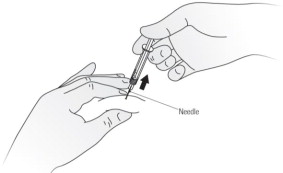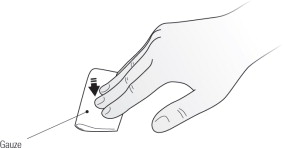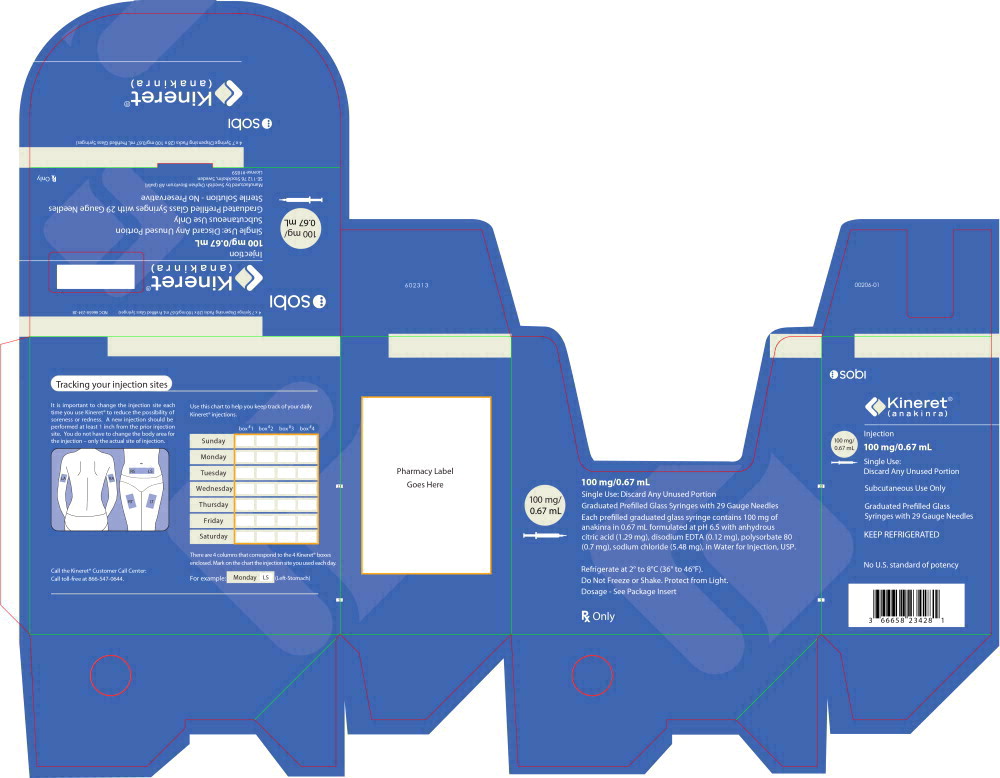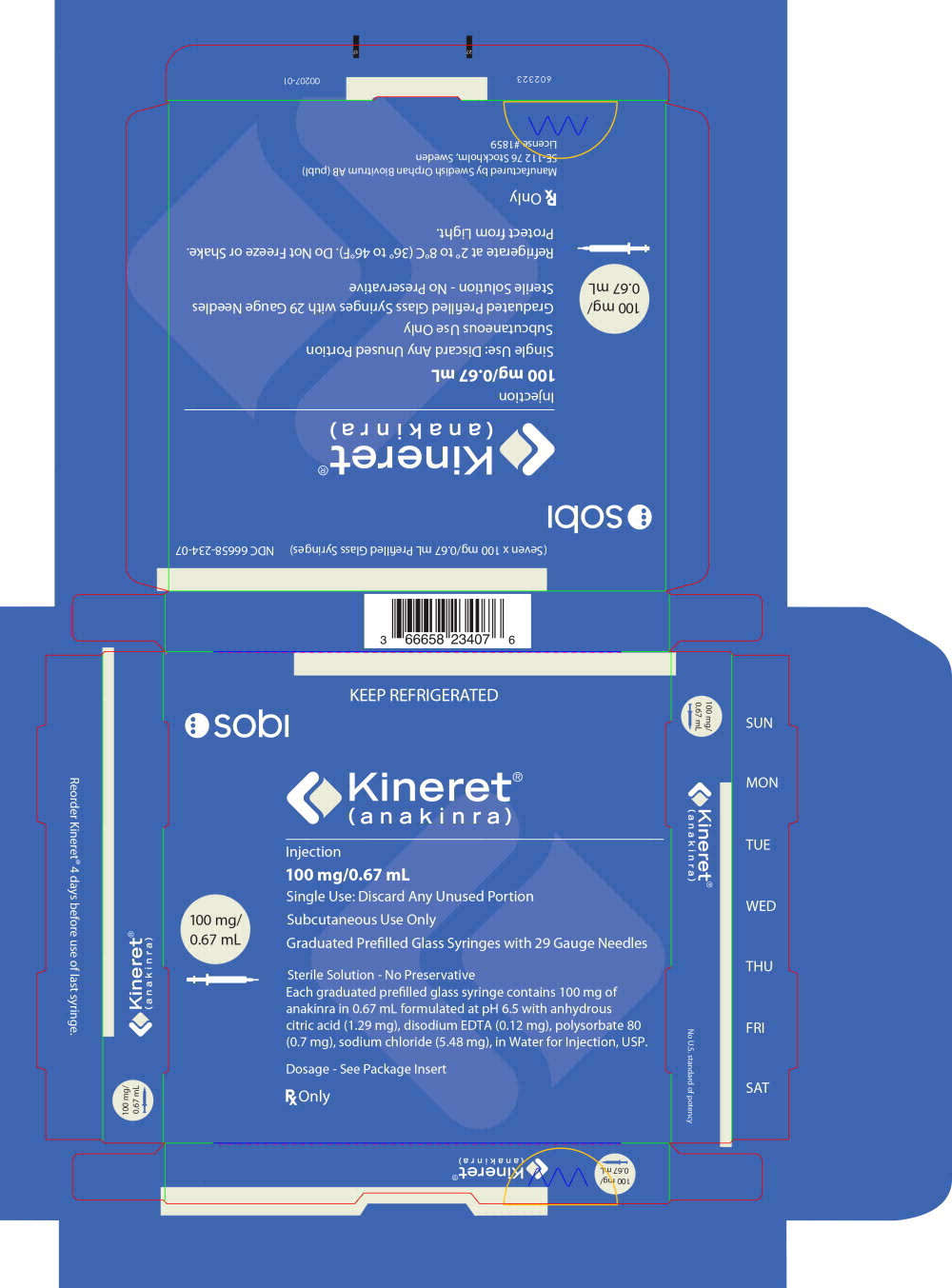 DRUG LABEL: Kineret
NDC: 66658-234 | Form: INJECTION, SOLUTION
Manufacturer: Swedish Orphan Biovitrum AB (publ)
Category: prescription | Type: HUMAN PRESCRIPTION DRUG LABEL
Date: 20251105

ACTIVE INGREDIENTS: ANAKINRA 100 mg/0.67 mL
INACTIVE INGREDIENTS: ANHYDROUS CITRIC ACID 1.29 mg/0.67 mL; SODIUM CHLORIDE 5.48 mg/0.67 mL; EDETATE DISODIUM 0.12 mg/0.67 mL; POLYSORBATE 80 0.7 mg/0.67 mL; WATER

HIGHLIGHTS OF PRESCRIBING INFORMATION

These highlights do not include all the information needed to use KINERET safely and effectively. See full prescribing information for KINERET.
KINERET® (anakinra) injection, for subcutaneous use
Initial U.S. Approval: 2001

RECENT MAJOR CHANGES

Dosage and Administration, Administration (2.5) 10/2025
Warnings and Precautions, Amyloidosis (5.5) 10/2025

1 INDICATIONS AND USAGE

KINERET is an interleukin-1 receptor antagonist indicated for:

Rheumatoid Arthritis (RA)

- Reduction in signs and symptoms and slowing the progression of structural damage in moderately to severely active rheumatoid arthritis, in patients 18 years of age or older who have failed 1 or more disease modifying antirheumatic drugs (DMARDs) (1.1)

Cryopyrin-Associated Periodic Syndromes (CAPS)

- Treatment of Neonatal-Onset Multisystem Inflammatory Disease (NOMID) (1.2)

Deficiency of Interleukin-1 Receptor Antagonist (DIRA)

- Treatment of Deficiency of Interleukin-1 Receptor Antagonist (DIRA) (1.3)

2 DOSAGE AND ADMINISTRATION

Rheumatoid Arthritis (RA)

- The recommended dose of KINERET for the treatment of patients with rheumatoid arthritis is 100 mg/day administered daily by subcutaneous injection. The dose should be administered at approximately the same time every day (2.1)
- Physicians should consider a dose of 100 mg of KINERET administered every other day for RA patients who have severe renal insufficiency or end stage renal disease (defined as creatinine clearance < 30 mL/min, as estimated from serum creatinine levels) (2.4)

Cryopyrin-Associated Periodic Syndromes (CAPS)

- The recommended starting dose of KINERET is 1-2 mg/kg daily for NOMID patients. The dose can be individually adjusted to a maximum of 8 mg/kg daily to control active inflammation. (2.2)
- Physicians should consider administration of the prescribed KINERET dose every other day for NOMID patients who have severe renal insufficiency or end stage renal disease (defined as creatinine clearance < 30 mL/min, as estimated from serum creatinine levels) (2.4)

Deficiency of Interleukin-1 Receptor Antagonist (DIRA)

- The recommended starting dose of KINERET is 1-2 mg/kg daily for patients with DIRA. The dose can be individually adjusted to a maximum of 8 mg/kg daily to control active inflammation. (2.3)
- Physicians should consider administration of the prescribed KINERET dose every other day for patients with DIRA who have severe renal insufficiency or end stage renal disease (defined as creatinine clearance < 30 mL/min, as estimated from serum creatinine levels) (2.4)

See full prescribing information for administration instructions (2.4)

3 DOSAGE FORMS AND STRENGTHS

Injection: 100 mg/0.67 mL solution in a single-use prefilled syringe for subcutaneous injection. Graduated syringe allows for doses between 20 mg and 100 mg. (3)

4 CONTRAINDICATIONS

Known hypersensitivity to E coli-derived proteins, Kineret, or to any component of the product. (4)

5 WARNINGS AND PRECAUTIONS

- In RA, discontinue use if serious infection develops. In KINERET-treated NOMID or DIRA patients, the risk of a disease flare when discontinuing KINERET treatment should be weighed against the potential risk of continued treatment. Do not initiate KINERET in patients with active infections. (5.1)
- Use in combination with Tumor Necrosis Factor (TNF) blocking agents is not recommended (5.2)
- Hypersensitivity reactions, including anaphylactic reactions and angioedema, and serious cutaneous reactions including Drug Reaction with Eosinophilia and Systemic Symptoms (DRESS) can occur; discontinue KINERET, treat promptly, and monitor until reaction resolves. Patients with DIRA may have an increased risk of allergic reactions, particularly in the first several weeks after starting KINERET treatment (5.3)
- The impact of treatment with KINERET on active and/or chronic infections and the development of malignancies is not known (5.4)
- Recommend patients to rotate injection sites to reduce the risk of injection site amyloid deposits (5.5)
- Live vaccines should not be given concurrently with KINERET (5.6)
- Neutrophil counts should be assessed prior to initiating KINERET treatment, and while receiving KINERET, monthly for 3 months, and thereafter quarterly for a period up to 1 year (5.7)

6 ADVERSE REACTIONS

Rheumatoid Arthritis (RA)

Most common adverse reactions (incidence ≥ 5%) are injection site reaction, worsening of rheumatoid arthritis, upper respiratory tract infection, headache, nausea, diarrhea, sinusitis, arthralgia, flu like-symptoms, and abdominal pain (6.1)

NOMID

The most common AEs during the first 6 months of treatment (incidence > 10%) are injection site reaction, headache, vomiting, arthralgia, pyrexia, and nasopharyngitis (6.2)

DIRA

The most common AEs are upper respiratory tract infections, rash, pyrexia, influenza like illness, and gastroenteritis (6.3)

To report SUSPECTED ADVERSE REACTIONS, contact Swedish Orphan Biovitrum at 1-866-547-0644 or FDA at 1-800-FDA-1088 or www.fda.gov/medwatch.

7 DRUG INTERACTIONS

- A higher rate of serious infections has been observed in RA patients treated with concurrent KINERET and etanercept therapy than in patients treated with etanercept alone. Use of KINERET in combination with TNF blocking agents is not recommended (7)

8 USE IN SPECIFIC POPULATIONS

- Pediatric use: KINERET is indicated for use in pediatric patients with NOMID and DIRA (8.4)
- Geriatric use: Because there is a higher incidence of infections in the elderly population in general, caution should be used in treating the elderly (8.5)
- Renal impairment: This drug is known to be substantially excreted by the kidney, and the risk of toxic reactions to this drug may be greater in patients with impaired renal function (8.6)

FULL PRESCRIBING INFORMATION

1 INDICATIONS AND USAGE

1.1 Active Rheumatoid Arthritis

KINERET is indicated for the reduction in signs and symptoms and slowing the progression of structural damage in moderately to severely active rheumatoid arthritis (RA), in patients 18 years of age or older who have failed 1 or more disease modifying antirheumatic drugs (DMARDs). KINERET can be used alone or in combination with DMARDs other than Tumor Necrosis Factor (TNF) blocking agents [see Warnings and Precautions (5.2)].

1.2 Cryopyrin-Associated Periodic Syndromes (CAPS)

KINERET is indicated for the treatment of Neonatal-Onset Multisystem Inflammatory Disease (NOMID).

1.3 Deficiency of Interleukin-1 Receptor Antagonist (DIRA)

KINERET is indicated for the treatment of Deficiency of Interleukin-1 Receptor Antagonist (DIRA)

2 DOSAGE AND ADMINISTRATION

2.1 Active Rheumatoid Arthritis

The recommended dose of KINERET for the treatment of patients with rheumatoid arthritis is 100 mg/day administered daily by subcutaneous injection. Higher doses did not result in a higher response. The dose should be administered at approximately the same time every day.

2.2 Cryopyrin-Associated Periodic Syndromes (CAPS)

The recommended starting dose of KINERET is 1-2 mg/kg for NOMID patients. The dose can be individually adjusted to a maximum of 8 mg/kg daily to control active inflammation.

Adjust doses in 0.5 to 1 mg/kg increments. Once daily administration is generally recommended, but the dose may be split into twice daily administrations. Each syringe is intended for a single use. A new syringe must be used for each dose. Any unused portion after each dose should be discarded.

2.3 Deficiency of Interleukin-1 Receptor Antagonist (DIRA)

The recommended starting dose of KINERET is 1-2 mg/kg daily for patients with DIRA. The dose can be individually adjusted to a maximum of 8 mg/kg daily to control active inflammation. Adjust doses in 0.5 to 1 mg/kg increments.

Each syringe is intended for a single use. A new syringe must be used for each dose. Any unused portion after each dose should be discarded.

2.4 Renal Impairment

Physicians should consider administration of the prescribed dose of KINERET every other day for patients who have severe renal insufficiency or end stage renal disease (defined as creatinine clearance < 30 mL/min, as estimated from serum creatinine levels) [see Use in Specific Populations (8.6) and Clinical Pharmacology (12.3)].

2.5 Administration

Instructions on appropriate use should be given by the healthcare provider to the patient or caregiver. Patients or caregivers should not be allowed to administer KINERET until the patient or caregiver has demonstrated a thorough understanding of procedures and an ability to inject the product correctly. The prescribed dose of KINERET should be administered according to the instructions for use and any unused portions discarded. After administration of KINERET it is essential to follow the proper procedure for disposal of syringes and any residual drug. Recommend patients to rotate their injection sites to reduce the risk of injection site reactions and injection site amyloid deposits [see Warnings and precautions (5.5)]. See the “Information for Patients” insert for detailed instructions on the handling and injection of KINERET.

Do not use KINERET beyond the expiration date shown on the carton. Visually inspect the solution for particulate matter and discoloration before administration. There may be trace amounts of small, translucent-to-white amorphous particles of protein in the solution. The prefilled syringe should not be used if the solution is discolored or cloudy, or if foreign particulate matter is present. If the number of translucent-to-white amorphous particles in a given syringe appears excessive, do not use this syringe.

3 DOSAGE FORMS AND STRENGTHS

Injection: 100 mg/0.67 mL solution in a single-use prefilled syringe for subcutaneous injection. Graduated syringe allows for doses between 20 and 100 mg.

4 CONTRAINDICATIONS

KINERET is contraindicated in patients with known hypersensitivity to E coli-derived proteins, KINERET, or any components of the product [see Hypersensitivity Reactions (5.3)].

5 WARNINGS AND PRECAUTIONS

5.1 Serious Infections

KINERET has been associated with an increased incidence of serious infections (2%) vs. Placebo (< 1%) in clinical trials in RA. Administration of KINERET in RA should be discontinued if a patient develops a serious infection. In KINERET treated NOMID and DIRA patients the risk of a disease flare when discontinuing KINERET treatment should be weighed against the potential risk of continued treatment. Treatment with KINERET should not be initiated in patients with active infections. The safety and efficacy of KINERET in immunosuppressed patients or in patients with chronic infections have not been evaluated.

Drugs that affect the immune system by blocking tumor necrosis factor (TNF) have been associated with an increased risk of reactivation of latent tuberculosis (TB). It is possible that taking drugs such as KINERET that blocks IL-1 increases the risk of TB or other atypical or opportunistic infections. Health care providers should follow current CDC guidelines both to evaluate for and to treat possible latent tuberculosis infections before initiating therapy with KINERET.

5.2 Use with TNF Blocking Agents

In a 24-week study of concurrent KINERET and etanercept therapy in RA patients, the rate of serious infections in the combination arm (7%) was higher than with etanercept alone (0%). The combination of KINERET and etanercept did not result in higher ACR response rates compared to etanercept alone [see Clinical Studies (14)]. Use of KINERET in combination with TNF blocking agents is not recommended.

5.3 Hypersensitivity Reactions

Hypersensitivity reactions, including anaphylactic reactions and angioedema, have been reported with KINERET. Serious cutaneous reactions, including Drug Reaction with Eosinophilia and Systemic Symptoms (DRESS), have been reported in patients with autoinflammatory conditions treated with KINERET. If a severe hypersensitivity reaction occurs, immediately discontinue KINERET; treat promptly and monitor until signs and symptoms resolve.

KINERET is the recombinant form of IL-1Ra that DIRA patients are lacking. Patients with DIRA may have an increased risk of allergic reactions, particularly in the first several weeks after starting KINERET treatment. Patients should be closely monitored during this time period. If a severe allergic reaction occurs, appropriate treatment should be initiated and discontinuation of KINERET should be considered.

5.4 Immunosuppression

The impact of treatment with KINERET on active and/or chronic infections and the development of malignancies is not known [see Adverse Reactions (6)] .

5.5 Amyloidosis

Post-marketing cases of injection site amyloid deposits [see Postmarketing Experience (6.4)] have been reported in NOMID patients after receiving high doses of Kineret injected subcutaneously into the same area of skin over long periods of time. Systemic AIL1RAP (IL-1 receptor antagonist protein) amyloidosis occurred in some of these patients with injection site amyloid deposits; these patients presented with proteinuria. Recommend patients to rotate their injection sites. In patients with confirmed injection site amyloid deposits, monitor proteinuria for systemic amyloidosis.

5.6 Immunizations

In a placebo-controlled clinical trial (n = 126), no difference was detected in anti-tetanus antibody response between the KINERET and placebo treatment groups when the tetanus/diphtheria toxoids vaccine was administered concurrently with KINERET. No data are available on the effects of vaccination with other inactivated antigens in patients receiving KINERET. No data are available on either the effects of live vaccination or the secondary transmission of infection by live vaccines in patients receiving KINERET. Therefore, live vaccines should not be given concurrently with KINERET.

5.7 Neutrophil Count

Patients receiving KINERET may experience a decrease in neutrophil counts. Neutrophil counts should therefore be assessed prior to initiating KINERET treatment, and while receiving KINERET, monthly for 3 months, and thereafter quarterly for a period up to 1 year.

In the placebo-controlled studies, 8% of RA patients receiving KINERET had decreases in neutrophil counts of at least one World Health Organization (WHO) toxicity grade compared with 2% in the placebo control group. Nine KINERET-treated patients (0.4%) experienced neutropenia (ANC < 1 x 10 ^9/L). This is discussed in more detail in the Adverse Reactions (6): Hematologic Events (6.1) section.

In 43 NOMID patients followed for up to 60 months 2 patients experienced neutropenia that resolved over time during continued KINERET treatment. [see Adverse Reactions (6.2)]

6 ADVERSE REACTIONS

Because clinical trials are conducted under widely varying conditions, adverse reaction rates observed in the clinical trials of a drug cannot be directly compared to rates in the clinical trials of another drug and may not reflect the rates observed in clinical practice.

6.1 Clinical Studies Experience in RA

The most serious adverse reactions were:

- Serious Infections – [see Warnings and Precautions (5.1)]
- Neutropenia, particularly when used in combination with TNF blocking agents

The most common adverse reaction with KINERET is injection-site reactions. These reactions were the most common reason for withdrawing from studies.

The data described herein reflect exposure to KINERET in 3025 patients, including 2124 exposed for at least 6 months and 884 exposed for at least one year. Studies 1 and 4 used the recommended dose of 100 mg per day. The patients studied were representative of the general population of patients with rheumatoid arthritis.

Injection-site Reactions

The most common and consistently reported treatment-related adverse event associated with KINERET is injection-site reaction (ISR). In Studies 1 and 4, 71% of patients developed an ISR, which was typically reported within the first 4 weeks of therapy. The majority of ISRs were reported as mild (72.6% mild, 24.1% moderate and 3.2% severe). The ISRs typically lasted for 14 to 28 days and were characterized by 1 or more of the following: erythema, ecchymosis, inflammation, and pain.

Injection-site Reactions

The most common and consistently reported treatment-related adverse event associated with KINERET is injection-site reaction (ISR). In Studies 1 and 4, 71% of patients developed an ISR, which was typically reported within the first 4 weeks of therapy. The majority of ISRs were reported as mild (72.6% mild, 24.1% moderate and 3.2% severe). The ISRs typically lasted for 14 to 28 days and were characterized by 1 or more of the following: erythema, ecchymosis, inflammation, and pain.

Injection-site Reactions

The most common and consistently reported treatment-related adverse event associated with KINERET is injection-site reaction (ISR). In Studies 1 and 4, 71% of patients developed an ISR, which was typically reported within the first 4 weeks of therapy. The majority of ISRs were reported as mild (72.6% mild, 24.1% moderate and 3.2% severe). The ISRs typically lasted for 14 to 28 days and were characterized by 1 or more of the following: erythema, ecchymosis, inflammation, and pain.

Infections

In Studies 1 and 4 combined, the incidence of infection was 39% in the KINERET-treated patients and 37% in placebo-treated patients during the first 6 months of blinded treatment. The incidence of serious infections in Studies 1 and 4 was 2% in KINERET-treated patients and 1% in patients receiving placebo over 6 months. The incidence of serious infection over 1 year was 3% in KINERET-treated patients and 2% in patients receiving placebo. These infections consisted primarily of bacterial events such as cellulitis, pneumonia, and bone and joint infections. Majority of patients (73%) continued on study drug after the infection resolved. No serious opportunistic infections were reported. Patients with asthma appeared to be at higher risk of developing serious infections when treated with KINERET (8 of 177 patients, 4.5%) compared to placebo (0 of 50 patients, 0%).

In open-label extension studies, the overall rate of serious infections was stable over time and comparable to that observed in controlled trials. In clinical studies and postmarketing experience, cases of opportunistic infections have been observed and included fungal, mycobacterial and bacterial pathogens. Infections have been noted in all organ systems and have been reported in patients receiving KINERET alone or in combination with immunosuppressive agents.

In patients who received both KINERET and etanercept for up to 24 weeks, the incidence of serious infections was 7%. The most common infections consisted of bacterial pneumonia (4 cases) and cellulitis (4 cases). One patient with pulmonary fibrosis and pneumonia died due to respiratory failure.

Malignancies

Among 5300 RA patients treated with KINERET in clinical trials for a mean of 15 months (approximately 6400 patient years of treatment), 8 lymphomas were observed for a rate of 0.12 cases/100 patient years. This is 3.6 fold higher than the rate of lymphomas expected in the general population, based on the National Cancer Institute's Surveillance, Epidemiology and End Results (SEER) database.^3An increased rate of lymphoma, up to several fold, has been reported in the RA population, and may be further increased in patients with more severe disease activity. Thirty-seven malignancies other than lymphoma were observed. Of these, the most common were breast, respiratory system, and digestive system. There were 3 melanomas observed in Study 4 and its long-term open-label extension, greater than the 1 expected case. The significance of this finding is not known. While patients with RA, particularly those with highly active disease, may be at a higher risk (up to several fold) for the development of lymphoma, the role of IL-1 blockers in the development of malignancy is not known.

Hematologic Events

In placebo-controlled studies with KINERET, 8% of patients receiving KINERET had decreases in total white blood counts of at least one WHO toxicity grade, compared with 2% of placebo patients. Nine KINERET-treated patients (0.4%) developed neutropenia (ANC < 1 x 10^9/L). 9 % of patients receiving KINERET had increases in eosinophil differential percentage of at least one WHO toxicity grade, compared with 3 % of placebo patients. Of patients treated concurrently with KINERET and etanercept 2% developed neutropenia (ANC < 1 x 10^9/L). While neutropenic, one patient developed cellulitis which recovered with antibiotic therapy. 2% of patients receiving KINERET had decreases in platelets, all of WHO toxicity grade one, compared to 0% of placebo patients.

Hypersensitivity Reactions

Hypersensitivity reactions including anaphylactic reactions, angioedema, urticaria, rash, and pruritus have been reported with KINERET.

Immunogenicity

As with all therapeutic proteins, there is potential for immunogenicity. In Studies 1 and 4, from which data is available for up to 36 months, 49% of patients tested positive for anti-anakinra binding antibodies at one or more time points using a biosensor assay. Of the 1615 patients with available data at Week 12 or later, 30 (2%) tested positive for neutralizing antibodies in a cell-based bioassay. Of the 13 patients with available follow-up data, 5 patients remained positive for neutralizing antibodies at the end of the studies. No correlation between antibody development and adverse events was observed.

The detection of antibody formation is highly dependent on the sensitivity and specificity of the assays. Additionally, the observed incidence of antibody (including neutralizing antibody) positivity in an assay may be influenced by several factors, including sample handling, concomitant medications, and underlying disease. For these reasons, comparison of the incidence of antibodies to KINERET with the incidence of antibodies to other products may be misleading.

Lipids

Cholesterol elevations were observed in some patients treated with KINERET.

Other Adverse Events

Table 1 reflects adverse events in Studies 1 and 4, that occurred with a frequency of ≥ 5% in KINERET-treated patients over a 6-month period.

Table 1: Percent of RA Patients Reporting Adverse Events (Studies 1 and 4)
 | Placebo |  |  | KINERET 100 mg/day
Preferred term | (n = 733) |  |  | (n = 1565)
Injection Site Reaction | 29% |  |  | 71%
Worsening of RA | 29% |  |  | 19%
Upper Respiratory Tract Infections | 17% |  |  | 14%
Headache | 9% |  |  | 12%
Nausea | 7% |  |  | 8%
Diarrhea | 5% |  |  | 7%
Sinusitis | 7% |  |  | 7%
Arthralgia | 6% |  |  | 6%
Flu Like Symptoms | 6% |  |  | 6%
Abdominal Pain | 5% |  |  | 5%

6.2 Clinical Study Experience in NOMID

The data described herein reflect an open-label study in 43 NOMID patients exposed to KINERET for up to 60 months adding up to a total exposure of 159.8 patient years.

Patients were treated with a starting dose of 1 to 2 mg/kg/day and an average maintenance dose of 3-4 mg/kg/day adjusted depending on the severity of disease. Among pediatric NOMID patients, doses up to 7.6 mg/kg/day have been maintained for up to 15 months.

There were 24 serious adverse events (SAEs) reported in 14 of the 43 treated patients. The most common type of SAEs reported were infections [see Warnings and Precautions (5.1)] . Five SAEs were related to lumbar puncture, which was part of the study procedure.

There were no permanent discontinuations of study drug treatment due to AEs. Doses were adjusted in 5 patients because of AEs; all were dose increases in connection with disease flares.

The reporting frequency of AEs was highest during the first 6 months of treatment. The incidence of AEs did not increase over time, and no new types of AEs emerged.

The most commonly reported AEs during the first 6 months of treatment (incidence >10%) were injection site reaction (ISR), headache, vomiting, arthralgia, pyrexia, and nasopharyngitis (Table 2).

The most commonly reported AEs during the 60-month study period, calculated as the number of events/patient years of exposure, were arthralgia, headache, pyrexia, upper respiratory tract infection, nasopharyngitis, and rash.

The AE profiles for different age groups <2 years, 2-11 years, and 12-17 years corresponded to the AE profile for patients ≥18 years, with the exception of infections and related symptoms being more frequent in patients <2 years.

Infections

The reporting rate for infections was higher during the first 6 months of treatment (2.3 infections/patient-year) compared to after the first 6 months (1.7 infections/patient year). The most common infections were upper respiratory tract infection, sinusitis, ear infections, and nasopharyngitis.

There were no deaths or permanent treatment discontinuations due to infections. In one patient KINERET administration was temporarily stopped during an infection and in 5 patients the dose of KINERET was increased due to disease flares in connection with infections. Thirteen infections in 7 patients were classified as serious, the most common being pneumonia and gastroenteritis occurring in 3 and 2 patients, respectively. No serious opportunistic infections were reported.

The reporting frequency for infections was highest in patients <12 years of age.

Hematologic Events

After start of KINERET treatment neutropenia was reported in 2 patients. One of these patients experienced an upper respiratory tract infection and an otitis media infection. Both episodes of neutropenia resolved over time with continued KINERET treatment.

Injection Site Reactions

In total, 17 injection site reactions (ISRs) were reported in 10 patients during the 60-month study period. Out of the 17 ISRs, 11 (65%) occurred during the first month and 13 (76%) were reported during the first 6 months. No ISR was reported after Year 2 of treatment. The majority of ISRs were reported as mild (76% mild, 24% moderate). No patient permanently or temporarily discontinued KINERET treatment due to injection site reactions.

Immunogenicity

The immunogenicity of KINERET in NOMID patients was not evaluated.

Table 2. Most common (>10% of patients) treatment-emergent adverse events during the first 6 months of KINERET treatment
 | Safety population
 | (N=43) Total exposure in patient years= 20.8
Preferred term | N (%) | Number of events /patient year
Injection site reaction | 7 (16.3%) | 0.5
Headache | 6 (14.0%) | 0.7
Vomiting | 6 (14.0%) | 0.6
Arthralgia | 5 (11.6%) | 0.6
Pyrexia | 5 (11.6%) | 0.4
Nasopharyngitis | 5 (11.6%) | 0.3

The most common adverse reactions occurring after the first 6-month period of treatment with KINERET (up to 60 months of treatment) included: arthralgia, headache, pyrexia, upper respiratory tract infection, nasopharyngitis, and rash.

6.3 Clinical Study Experience in DIRA

The safety data described in this section reflect exposure to KINERET in 9 patients with DIRA treated for up to 10 years in a natural history study (study 17-I-0016). Most patients received a starting dose of 1 to 2 mg/kg/day and thereafter doses were individually adjusted to reach a stable efficacious dose. The highest dose given was 7.5 mg/kg/day. Overall, the safety profile observed in patients with DIRA treated with KINERET was consistent with the safety profile in NOMID patients.

There were 16 serious adverse events (SAEs) reported in 4 out of 9 treated patients. The most common type of SAEs reported (5 events in 2 patients) were infections [see Warnings and Precautions (5.1)] .

The most common adverse events in patients with DIRA were upper respiratory tract infections, rash, pyrexia, influenza like illness and gastroenteritis.

There were no permanent discontinuations of KINERET treatment due to AEs.

Infections

There were 16 infections in 5 patients (reporting rate: 0.28 infections / patient year). The most common infections were upper respiratory tract infections, cellulitis and gastroenteritis.

Hypersensitivity Reactions

One patient with DIRA had a serious event of urticaria on day 10 of KINERET treatment [see Warnings and Precautions (5.3)] .

Injection Site Reactions

There was one report of injection site pain, which did not cause discontinuation of KINERET treatment.

6.4 Postmarketing Experience

The following adverse reactions have been identified during postapproval use of KINERET. Because these reactions are reported voluntarily from a population of uncertain size, it is not always possible to reliably estimate their frequency or establish a causal relationship to drug exposure.

Hepato-biliary disorders:

- elevations of transaminases,
- non-infectious hepatitis

Hematologic events:

- thrombocytopenia, including severe thrombocytopenia (i.e platelet counts <10x10 ^9/L)

Skin and subcutaneous tissue disorders:

- Drug Reaction with Eosinophilia and Systemic Symptoms (DRESS) [see Warnings & Precautions (5.3)]
- injection site amyloid deposits [see Warnings & Precautions (5.5)]

7 DRUG INTERACTIONS

No drug-drug interaction studies in human subjects have been conducted. Toxicologic and toxicokinetic studies in rats did not demonstrate any alterations in the clearance or toxicologic profile of either methotrexate or KINERET when the two agents were administered together.

7.1 TNF Blocking Agents

A higher rate of serious infections has been observed in patients treated with concurrent KINERET and etanercept therapy than in patients treated with etanercept alone [see Warnings and Precautions (5.2)] . Two percent of patients treated concurrently with KINERET and etanercept developed neutropenia (ANC < 1 x 10 ^9/L). Use of KINERET in combination with TNF blocking agents is not recommended.

8 USE IN SPECIFIC POPULATIONS

8.1 Pregnancy

Risk Summary

Available data from retrospective studies and case reports on KINERET use in pregnant women are insufficient to identify a drug associated risk of major birth defects, miscarriage, or maternal and fetal adverse events. There are risks to the mother and fetus associated with active rheumatoid arthritis or Cryopyrin-Associated Periodic Syndromes (CAPS). In animal reproduction studies, subcutaneous administration of anakinra to pregnant rats and rabbits during organogenesis demonstrated no evidence of fetal harm at doses up to 25 times the maximum recommended human dose (MRHD).

The estimated background risk of major birth defects and miscarriage for the indicated population is unknown. All pregnancies have a background risk of birth defect, loss, or other adverse outcomes. In the U.S. general population, the estimated background risk of major birth defects and miscarriage in clinically recognized pregnancies is 2-4% and 15-20%, respectively.

Clinical Considerations

Disease-associated maternal and/or embryo/fetal risk

Published data suggest the risk of adverse pregnancy outcomes in women with rheumatoid arthritis or CAPS is associated with increased disease activity. Adverse pregnancy outcomes include preterm delivery (before 37 weeks of gestation), low birth weight (<2500 grams), and small for gestational age at birth.

Data

Human Data

The available data from retrospective studies and case reports of anakinra-exposed pregnancies have not identified an increased frequency or pattern of birth defects, miscarriage, or adverse maternal or fetal outcomes. An international multi-center retrospective study of pregnancy outcomes with interleukin-1 inhibitors reported on 23 anakinra-exposed pregnancies. There were 21 live births of healthy infants, 1 miscarriage, and 1 infant with left renal agenesis. The estimated background rate of detected renal malformations is 0.2-2% of all newborns. Another retrospective study reported on 10 anakinra-exposed pregnancies in women with CAPS. There were 9 live births, 1 miscarriage, and 1 fetal demise in a twin pregnancy. The surviving twin was born healthy. Overall, these data cannot definitively establish or exclude any anakinra-associated risks during pregnancy. Methodological limitations of these data include small sample size and the inability to control for confounders such as the timing of drug exposure, underlying maternal disease, and concomitant medication use.

Animal Data

Animal reproduction studies were conducted in rats and rabbits. In embryo-fetal development studies, anakinra was administered throughout the period of organogenesis at the subcutaneous doses of 12.5, 50, and 200 mg/kg/day to pregnant rats from gestation days (GD) 7 to 17 and pregnant rabbits from GD 6 to 18. In these studies, anakinra at doses up to 25 times the MRHD (on a mg/kg basis at maternal subcutaneous doses up to 200 mg/kg/day) revealed no evidence of harm to the fetus.

8.2 Lactation

Risk Summary

There are no data on the presence of anakinra in either human or animal milk or the effects on milk production. Available published data from a small retrospective study and postmarketing case reports do not establish an association between maternal anakinra use during lactation and adverse effects on breastfed infants. The limited clinical data during lactation precludes a clear determination of the risk of KINERET to an infant during lactation. Therefore, the developmental and health benefits of breastfeeding should be considered along with the mother's clinical need for KINERET and any potential adverse effects on the breastfed infant from KINERET or from the underlying maternal condition.

8.4 Pediatric Use

PEDIATRIC USE

Neonatal-Onset Multisystem Inflammatory Disease (NOMID)

The NOMID study included 36 pediatric patients: 13 below 2 years, 18 between 2 and 11 years, and 5 between 12 and 17 years of age. A subcutaneous KINERET starting dose of 1–2 mg/kg/day was administered in all age groups. An average maintenance dose of 3–4 mg/kg/day was adequate to maintain clinical response throughout the study irrespective of age but a higher dose was, on occasion, required in severely affected patients. The prefilled syringe does not allow doses lower than 20 mg to be administered.

PEDIATRIC USE

Deficiency of Interleukin-1 Receptor Antagonist (DIRA)

The study in DIRA patients included 9 pediatric patients (ages 1 month to 9 years at start of KINERET treatment). Most patients received a starting dose of 1 to 2 mg/kg/day. Doses up to 7.5 mg/kg/day were given. The prefilled syringe does not allow doses lower than 20 mg to be administered.

PEDIATRIC USE

Juvenile Rheumatoid Arthritis (JRA)

The safety and effectiveness of KINERET in the treatment of pediatric patients with Juvenile Rheumatoid Arthritis (JRA) have not been established. KINERET was studied in a single randomized, blinded multi-center trial in 86 patients with polyarticular course JRA; ages 2-17 years receiving a dose of 1 mg/kg subcutaneously daily, up to a maximum dose of 100 mg. The 50 patients who achieved a clinical response after a 12-week open-label run-in were randomized to KINERET (25 patients) or placebo (25 patients), administered daily for an additional 16 weeks. A subset of these patients continued open-label treatment with KINERET for up to 1 year in a companion extension study. An adverse event profile similar to that seen in adult RA patients was observed in these studies. These study data are insufficient to demonstrate efficacy and, therefore, KINERET is not recommended for pediatric use in JRA.

8.5 Geriatric Use

A total of 752 RA patients ≥ 65 years of age, including 163 patients ≥ 75 years of age, were studied in clinical trials. No differences in safety or effectiveness were observed between these patients and younger patients, but greater sensitivity of some older individuals cannot be ruled out. Because there is a higher incidence of infections in the elderly population in general, caution should be used in treating the elderly.

This drug is known to be substantially excreted by the kidney, and the risk of toxic reactions to this drug may be greater in patients with impaired renal function.

8.6 Renal Impairment

This drug is known to be substantially excreted by the kidney, and the risk of toxic reactions to this drug may be greater in patients with impaired renal function [see Clinical Pharmacology (12.3)] .

8.7 Hepatic Impairment

No formal studies have been conducted examining the pharmacokinetics of KINERET administered subcutaneously in patients with hepatic impairment.

10 OVERDOSAGE

There have been no cases of overdose reported with KINERET in clinical trials of RA or NOMID. In sepsis trials no serious toxicities attributed to KINERET were seen when administered at mean calculated doses of up to 35 times those given patients with RA over a 72-hour treatment period.

11 DESCRIPTION

KINERET (anakinra) is a recombinant, nonglycosylated form of the human interleukin-1 receptor antagonist (IL-1Ra). KINERET differs from native human IL-1Ra in that it has the addition of a single methionine residue at its amino terminus. KINERET consists of 153 amino acids and has a molecular weight of 17.3 kilodaltons. It is produced by recombinant DNA technology using an E coli bacterial expression system.

KINERET is supplied in single use prefilled glass syringes with 29 gauge needles as a sterile, clear, colorless-to-white, preservative free solution for daily subcutaneous (SC) administration. The solution may contain trace amounts of small, translucent-to-white amorphous proteinaceous particles. Each prefilled glass syringe contains: 0.67 mL (100 mg) of anakinra in a solution (pH 6.5) containing anhydrous citric acid (1.29 mg), disodium EDTA (0.12 mg), polysorbate 80 (0.70 mg), and sodium chloride (5.48 mg) in Water for Injection, USP.

The prefilled syringe contains an outer rigid plastic needle shield attached to an inner needle cover. The syringe or needle shield components are not made with natural rubber latex.

12 CLINICAL PHARMACOLOGY

12.1 Mechanism of Action

KINERET blocks the biologic activity of IL-1 alpha and beta by competitively inhibiting IL-1 binding to the interleukin-1 type I receptor (IL-1RI), which is expressed in a wide variety of tissues and organs.

IL-1 production is induced in response to inflammatory stimuli and mediates various physiologic responses including inflammatory and immunological responses. IL-1 has a broad range of activities including cartilage degradation by its induction of the rapid loss of proteoglycans, as well as stimulation of bone resorption. The levels of the naturally occurring IL-1Ra in synovium and synovial fluid from RA patients are not sufficient to compete with the elevated amount of locally produced IL-1.

Spontaneous mutations in the CIAS1/NLRP3 gene have been identified in a majority of patients with cryopyrin-associated periodic syndromes such as NOMID. CIAS1/NLRP3 encodes for cryopyrin, a component of the inflammasome. The activated inflammasome results in proteolytic maturation and secretion of IL-1β, which has an important role in the systemic inflammation and manifestations of NOMID.

DIRA is an autosomal recessive monogenic autoinflammatory disease caused by mutations in the IL1RN gene leading to loss of secretion of the interleukin-1 receptor antagonist (IL-1Ra). The deficiency of IL-1Ra results in unopposed IL-1α and IL-1β pro-inflammatory signaling causing systemic inflammation with skin and bone involvement.

12.3 Pharmacokinetics

The absolute bioavailability of KINERET after a 70 mg subcutaneous bolus injection in healthy subjects (n = 11) is 95%. In subjects with RA, maximum plasma concentrations of KINERET occurred 3 to 7 hours after subcutaneous administration of KINERET at clinically relevant doses (1 to 2 mg/kg; n = 18); the terminal half-life ranged from 4 to 6 hours. In RA patients, no unexpected accumulation of KINERET was observed after daily subcutaneous doses for up to 24 weeks.

The influence of demographic covariates on the pharmacokinetics of KINERET was studied using population pharmacokinetic analysis encompassing 341 patients receiving daily subcutaneous injection of KINERET at doses of 30, 75, and 150 mg for up to 24 weeks. The estimated KINERET clearance increased with increasing creatinine clearance and body weight. After adjusting for creatinine clearance and body weight, gender and age were not significant factors for mean plasma clearance.

In NOMID patients, at a median SC dose of 3 mg/kg once daily and a median treatment time of 3.5 years, the median (range) steady-state serum exposure of anakinra was Cmax 3628 (655–8511) ng/mL (n=16) and C24h 203 (53–1979) ng/mL (n=16). The median (range) half-life of anakinra was 5.7 (3.1–28.2) hours (n=12). There was no obvious gender difference.

Patients With Renal Impairment: The mean plasma clearance of KINERET in subjects with mild (creatinine clearance 50-80 mL/min) and moderate (creatinine clearance 30-49 mL/min) renal insufficiency was reduced by 16% and 50%, respectively. In severe renal insufficiency and end stage renal disease (creatinine clearance < 30 mL/min^1), mean plasma clearance declined by 70% and 75%, respectively. Less than 2.5% of the administered dose of KINERET was removed by hemodialysis or continuous ambulatory peritoneal dialysis. Based on these observations, a dose schedule change should be considered for subjects with severe renal insufficiency or end stage renal disease [see Dosage and Administration (2.2)] .

Patients with Hepatic Dysfunction: No formal studies have been conducted examining the pharmacokinetics of KINERET administered subcutaneously in patients with hepatic impairment.

13 NONCLINICAL TOXICOLOGY

13.1 Carcinogenesis, Mutagenesis, and Impairment of Fertility

Long-term animal studies to evaluate the carcinogenic potential of KINERET were not conducted. KINERET had no effects on fertility and reproductive performance indices in male and female rats subcutaneous doses up to 200 mg/kg/day (approximately 25 times theMRHD on a mg/kg basis).

14 CLINICAL STUDIES

14.1 Clinical Studies in RA

The safety and efficacy of KINERET have been evaluated in three randomized, double-blind, placebo-controlled trials of 1790 patients ≥ 18 years of age with active rheumatoid arthritis (RA). An additional fourth study was conducted to assess safety. In the efficacy trials, KINERET was studied in combination with other disease-modifying antirheumatic drugs (DMARDs) other than Tumor Necrosis Factor (TNF) blocking agents (Studies 1 and 2) or as a monotherapy (Study 3).

Study 1 involved 899 patients with active RA who had been on a stable dose of methotrexate (MTX) (10 to 25 mg/week) for at least 8 weeks. All patients had at least 6 swollen/painful and 9 tender joints and either a C-reactive protein (CRP) of ≥ 1.5 mg/dL or an erythrocyte sedimentation rate (ESR) of ≥ 28 mm/hr. Patients were randomized to KINERET or placebo in addition to their stable doses of MTX. The first 501 patients were evaluated for signs and symptoms of active RA. The total 899 patients were evaluated for progression of structural damage.

Study 2 evaluated 419 patients with active RA who had received MTX for at least 6 months including a stable dose (15 to 25 mg/week) for at least 3 consecutive months prior to enrollment. Patients were randomized to receive placebo or one of five doses of KINERET subcutaneous daily for 12 to 24 weeks in addition to their stable doses of MTX.

Study 3 evaluated 472 patients with active RA and had similar inclusion criteria to Study 1 except that these patients had received no DMARD for the previous 6 weeks or during the study. Patients were randomized to receive either KINERET or placebo. Patients were DMARD-naïve or had failed no more than 3 DMARDs.

Study 4 was a placebo-controlled, randomized trial designed to assess the safety of KINERET in 1414 patients receiving a variety of concurrent medications for their RA including some DMARD therapies, as well as patients who were DMARD-free. The TNF blocking agents etanercept and infliximab were specifically excluded. Concurrent DMARDs included MTX, sulfasalazine, hydroxychloroquine, gold, penicillamine, leflunomide, and azathioprine. Unlike Studies 1, 2 and 3, patients predisposed to infection due to a history of underlying disease such as pneumonia, asthma, controlled diabetes, and chronic obstructive pulmonary disease (COPD) were also enrolled [see Adverse Reactions (6)] .

In Studies 1, 2 and 3, the improvement in signs and symptoms of RA was assessed using the American College of Rheumatology (ACR) response criteria (ACR 20, ACR 50, ACR 70). In these studies, patients treated with KINERET were more likely to achieve an ACR 20 or higher magnitude of response (ACR 50 and ACR 70) than patients treated with placebo (Table 3). The treatment response rates did not differ based on gender or ethnic group. The results of the ACR component scores in Study 1 are shown in Table 4.

Most clinical responses, both in patients receiving placebo and patients receiving KINERET, occurred within 12 weeks of enrollment.

Table 3: Percent of Patients with ACR Responses in Studies 1 and 3
 | Study 1 (Patients on MTX) |  | Study 3 (No DMARDs)
 |  |  |  | KINERET
Response | Placebo (n = 251) | KINERET 100 mg/day (n = 250) | Placebo (n = 119) | 75 mg/day (n = 115) | 150 mg/day (n = 115)
ACR 20 Month 3 Month 6 | 24% 22% | 34% a 38% c | 23% 27% | 33% 34% | 33% 43% a
ACR 50 Month 3 Month 6 | 6% 8% | 13% b 17% b | 5% 8% | 10% 11% | 8% 19% a
ACR 70 Month 3 Month 6 | 0% 2% | 3% a 6% a | 0% 1% | 0% 1% | 0% 1%
ap < 0.05, KINERET versus placebo
bp < 0.01, KINERET versus placebo
cp < 0.001, KINERET versus placebo

Table 4: Median ACR Component Scores in Study 1
 |  | Placebo/MTX |  |  | KINERET/MTX 100 mg/day
 |  | (n = 251) |  |  | (n = 250)
Parameter (median) |  | Baseline | Month 6 |  | Baseline | Month 6
Patient Reported Outcomes
 | Disability index a | 1.38 | 1.13 |  | 1.38 | 1.00
 | Patient global assessment b | 51.0 | 41.0 |  | 51.0 | 29.0
 | Pain b | 56.0 | 44.0 |  | 63.0 | 34.0
Objective Measures
 | ESR (mm/hr) | 35.0 | 32.0 |  | 36.0 | 19.0
 | CRP (mg/dL) | 2.2 | 1.6 |  | 2.2 | 0.5
Physician's Assessments
 | Tender/painful joints c | 20.0 | 11.0 |  | 23.0 | 9.0
 | Physician global assessment b | 59.0 | 31.0 |  | 59.0 | 26.0
 | Swollen joints d | 18.0 | 10.5 |  | 17.0 | 9.0
aHealth Assessment Questionnaire; 0 = best, 3 = worst; includes eight categories: dressing and grooming, arising, eating, walking, hygiene, reach, grip, and activities.
bVisual analog scale; 0 = best, 100 = worst
cScale 0 to 68
dScale 0 to 66

A 24-week study was conducted in 242 patients with active RA on background methotrexate who were randomized to receive either etanercept alone or the combination of KINERET and etanercept. The ACR 50 response rate was 31% for patients treated with the combination of KINERET and etanercept and 41% for patients treated with etanercept alone, indicating no added clinical benefit of the combination over etanercept alone. Serious infections were increased with the combination compared to etanercept alone [see Warnings and Precautions (5.1)] .

In Study 1, the effect of KINERET on the progression of structural damage was assessed by measuring the change from baseline at month 12 in the Total Modified Sharp Score (TSS) and its subcomponents, erosion score, and joint space narrowing (JSN) score. ^2 Radiographs of hands/wrists and forefeet were obtained at baseline, 6 months and 12 months and scored by readers who were unaware of treatment group. A difference between placebo and KINERET for change in TSS, erosion score (ES) and JSN score was observed at 12 months (Table 5).

Table 5: Mean Radiographic Changes Over 12 Months in Study 1
 | Placebo/MTX (N = 450) |  | KINERET 100 mg/day /MTX (N = 449) |  | Placebo/MTX vs. KINERET/MTX
 | Baseline | Change at Month 12 | Baseline | Change at Month 12 | 95% Confidence Interval* | p-value**
TSS | 52 | 2.6 | 50 | 1.7 | 0.9 [0.3, 1.6] | < 0.001
Erosion | 28 | 1.6 | 25 | 1.1 | 0.5 [0.1, 1.0] | 0.024
JSN | 24 | 1.1 | 25 | 0.7 | 0.4 [0.1, 0.7] | < 0.001
* Differences and 95% confidence intervals for the differences in change scores between Placebo/MTX and KINERET/MTX
** Based on Wilcoxon rank-sum test

The disability index of the Health Assessment Questionnaire (HAQ) was administered monthly for the first six months and quarterly thereafter during Study 1. Health outcomes were assessed by the Short Form-36 (SF-36) questionnaire. The 1-year data on HAQ in Study 1 showed more improvement with KINERET than placebo. The physical component summary (PCS) score of the SF-36 also showed more improvement with KINERET than placebo but not the mental component summary (MCS).

14.2 Clinical Studies in NOMID

The efficacy of KINERET was evaluated in a prospective, long-term, open-label and uncontrolled study which incorporated a withdrawal period in a subset of 11 patients. This study included 43 NOMID patients 0.7 to 46 years of age treated for up to 60 months. Patients were given an initial KINERET dose of 1–2.4 mg/kg body weight. During the study, the dose was adjusted by 0.5 to 1 mg/kg increments to a protocol-specified maximum of 10 mg/kg daily, titrated to control signs and symptoms of disease. The maximum dose actually studied was 7.6 mg/kg/day. The average maintenance dose was 3 to 4 mg/kg daily. In general, the dose was given once daily, but for some patients, the dose was split into twice daily administrations for better control of disease activity.

NOMID symptoms were assessed with a disease-specific Diary Symptom Sum Score (DSSS), which included the prominent disease symptoms fever, rash, joint pain, vomiting, and headache. In addition, serum amyloid A (SAA), hsCRP, and ESR levels were monitored. Changes in clinical and laboratory parameters from baseline to Months 3 to 6 and from Month 3 (before withdrawal) to the end of the withdrawal period were assessed in the subset of patients who underwent withdrawal. The estimated changes from baseline in DSSS are summarized through Month 60 in Table 6. Results were consistent across all subgroups, including age, gender, presence of CIAS1 mutation, and disease phenotype. Improvements occurred in all individual disease symptoms comprising the DSSS (Table 7), as well as in the serum markers of inflammation. For the 11 patients who went through a withdrawal phase, disease symptoms and serum markers of inflammation worsened after withdrawal and promptly responded to reinstitution of KINERET therapy. Upon withdrawal of treatment, the median time until disease flare criteria were met was 5 days.

Table 6. Estimated change from baseline in DSSS in NOMID patients (N=29)
Time point | Estimated mean change from baseline in DSSS* | 95% confidence interval
Month 3-6 | -3.5 | -3.7 to -3.3
Month 12 | -3.6 | -3.9 to -3.3
Month 36 | -3.5 | -3.8 to -3.2
Month 60 | -3.5 | -3.8 to -3.1
*Mean (SD) baseline value was 4.5 (3.2)

Table 7. Individual diary key symptom scores by visit (ITT diary population)
Visit (month) | Number of patients | Fever score* | Rash score* | Joint pain score* | Vomiting score* | Headache score*
Baseline | 29 | 0.5 (0.8) | 1.9 (1.1) | 1.2 (1.1) | 0.1 (0.2) | 0.9 (1.0)
1 | 28 | 0.1 (0.1) | 0.3 (0.5) | 0.2 (0.3) | 0.0 (0.0) | 0.2 (0.3)
3 | 26 | 0.1 (0.2) | 0.1 (0.2) | 0.2 (0.4) | 0.0 (0.1) | 0.1 (0.2)
6 | 25 | 0.0 (0.1) | 0.1 (0.1) | 0.2 (0.4) | 0.0 (0.1) | 0.2 (0.3)
12 | 24 | 0.1 (0.1) | 0.1 (0.2) | 0.1 (0.2) | 0.0 (0.1) | 0.1 (0.2)
36 | 19 | 0.0 (0.2) | 0.0 (0.2) | 0.1 (0.3) | 0.0 (0.0) | 0.2 (0.6)
60 | 15 | 0.0 (0.0) | 0.1 (0.3) | 0.3 (0.7) | 0.0 (0.0) | 0.1 (0.3)
*mean (SD)

KINERET treatment also appeared to be associated with improvement of, or stability in, assessments of other NOMID disease manifestations, such as CNS, audiogram, and visual acuity data, up to Month 60.

14.3 Clinical Studies in DIRA

The safety and efficacy of KINERET were evaluated in a long-term natural history study including 9 DIRA patients (ages 1 month to 9 years at the start of KINERET treatment) treated with KINERET for up to 10 years. All patients had genetically confirmed DIRA. The starting dose of KINERET was 1 to 2 mg/kg/day in the 6 patients for which the dose was reported. The dose was then individually adjusted to reach a stable efficacious dose to control active inflammation. The highest KINERET dose studied was 7.5 mg/kg/day. At the last visit during the first KINERET treatment period, the dose ranged between 2.2 and 6.1 mg/kg/day. Inflammatory remission was defined as achievement of all of the following criteria: CRP ≤ 5 mg/L, no pustulosis, no inflammatory bone disease, and no concomitant glucocorticosteroid use. All 9 patients achieved inflammatory remission while on KINERET treatment.

15 REFERENCES

1. Cockcroft DW and Gault HM. Prediction of creatinine clearance from serum creatinine. Nephron1976; 16:31-41.
2. Sharp JT, Young DY, Bluhm GB, et al. How many joints in the hands and wrists should be included in a score of radiologic abnormalities used to assess rheumatoid arthritis? Arthritis Rheum.1985; 28:1326-1335.
3. National Cancer Institute. Surveillance, Epidemiology, and End Results Database (SEER) Program. SEER Incidence Crude Rates, 11 Registries, 1992-1999.

16 HOW SUPPLIED/STORAGE AND HANDLING

KINERET is supplied in single-use preservative free, prefilled glass syringes with 29 gauge needles. Each prefilled glass syringe contains 100 mg of anakinra per 0.67 mL. The full syringe contains 100 mg anakinra. KINERET is dispensed in a 1 x 7 syringe dispensing pack containing 7 syringes (NDC 66658-234-07).

Storage

KINERET should be stored in the refrigerator at 2°C to 8°C (36°F to 46°F). DO NOT FREEZE OR SHAKE. Protect from light.

Rx only

17 PATIENT COUNSELING INFORMATION

Advise the patient to read the FDA-approved patient labeling (Patient Information and Instructions for Use).

Instruct patients and their caregivers on the proper dosage and administration of KINERET and provide all patients with the “Patient information and Instructions for Use” insert. While this Patient Information and Instructions for Use provides information about the product and its use, it is not intended to take the place of regular discussions between the patient and healthcare provider. The ability to inject subcutaneously should be assessed to ensure proper administration of KINERET. Thoroughly instruct patients and their caregivers on the importance of proper disposal and caution against the reuse of needles, syringes, and drug product. A puncture-resistant container for the disposal of used syringes should be available to the patient. The full container should be disposed of according to the directions provided by the healthcare provider.

Infections: Inform patients that KINERET may lower the ability of their immune system to fight infections. Advise patients of the importance of contacting their doctor if they develop any symptoms of infection.

Injection-site reactions: Physicians should explain to patients that almost a quarter of patients in the clinical trial experienced a reaction at the injection site. Injection-site reactions may include pain, erythema, swelling, pruritus, bruising, mass, inflammation, dermatitis, edema, urticaria, vesicles, warmth, and hemorrhage. Inform patients or their caregivers that the prefilled syringe should be removed from refrigeration and left at room temperature for 30 minutes before injecting. Patients should be advised to rotate the injection site and to avoid injecting into an area that is already swollen or red. Any persistent reaction should be brought to the attention of the prescribing physician.

Hypersensitivity reactions: Inform patients that serious allergic and skin reactions have been reported with KINERET. Advise patients to stop taking KINERET and seek immediate medical attention if they experience any symptoms suggesting allergic reactions (including rash, hives, and swelling of the face, lips, tongue, and throat that may cause difficulty in breathing or swallowing). Inform patients with DIRA and their caregivers, that DIRA patients may have an increased risk of allergic reactions, particularly in the first several weeks of treatment and they should be monitored closely.

sobi
SWEDISH ORPAHN BIOVITRUM

Manufactured by:
Swedish Orphan Biovitrum AB (publ)
SE-112 76 Stockholm, Sweden

U.S. License No. 1859

© Swedish Orphan Biovitrum AB (publ). All rights reserved.

The product, its production and/or its use may be covered by one or more US Patents, including US Patent Nos. 6,599,873 and 6,858,409 as well as other patents or patents pending.

Patient Information
KINERET® (KIN-eh-ret)
(anakinra)
injection, for subcutaneous use

What is KINERET?
KINERET is a prescription medicine called an interleukin-1 receptor antagonist (IL-1Ra) used to:

- Reduce the signs and symptoms and slow the damage of moderate to severe active rheumatoid arthritis (RA) in people age 18 years and older when 1 or more other medicines for RA have not worked.
- Treat people with a form of Cryopyrin-Associated Periodic Syndromes (CAPS) called Neonatal-Onset Multisystem Inflammatory Disease (NOMID).
- Treat people with Deficiency of Interleukin-1 Receptor Antagonist (DIRA).

KINERET is not for children with Juvenile Rheumatoid Arthritis.

Do not use KINERET if you are allergic to:

- proteins made from bacteria called E.Coli. Ask your healthcare provider if you are not sure.
- anakinra or any of the ingredients in KINERET. See the end of this leaflet for a complete list of ingredients in KINERET.

Before you use KINERET, tell your healthcare provider about all of your medical conditions, including if you:

- have an infection, a history of infections that keep coming back or other problems that can increase your risk of infections.
- are scheduled to receive any vaccines. People using KINERET should not receive live vaccines.
- have kidney problems.
- are pregnant or plan to become pregnant. It is not known if KINERET will harm your unborn baby.
- are breastfeeding or plan to breastfeed. It is not known if KINERET passes into your breast milk. You and your healthcare provider should decide if you will use KINERET or breastfeed.

Tell your healthcare provider about all the medicines you take, including prescription and over-the-counter medicines, vitamins, and herbal supplements.
KINERET and other medicines may affect each other and cause serious side effects.
Especially, tell your healthcare provider if you take certain other medicines that:

- affect your immune system called Tumor Necrosis Factor (TNF) blockers

Ask your healthcare provider for a list of these medicines if you are not sure.
Know the medicines you take. Keep a list of your medicines and show it to your healthcare provider and pharmacist when you get a new prescription.

How should I use KINERET?

- Read the Instructions for Use at the end of this Patient Information for information about the right way to use KINERET.
- Use KINERET exactly as your healthcare provider tells you to.
- You may not have to use all of the liquid medicine in the prefilled syringe. Your healthcare provider will show you how to find the correct dose of KINERET for you or your child.
- KINERET is given by injection under your skin.
- Inject KINERET at about the same time each day.
- If you have a kidney problem your healthcare provider may need to change how often you use your KINERET injections.
- If you miss a dose of KINERET, talk to your healthcare provider to find out when you should use your next injection.

What are the possible side effects of KINERET?
KINERET may cause serious side effects, including:

- serious infections. KINERET may lower your ability to fight infections. During your treatment with KINERET, call your healthcare provider right away if you:
  - get an infection.
  - have any sign of an infection including a fever or chills.
  - have any open sores on your body.
  You may get an infection if you receive live vaccines while you use KINERET. You should not receive live vaccines while you use KINERET.
- serious allergic reactions. Stop using KINERET, call your healthcare provider and, get emergency help right away if you have any of these symptoms of a serious allergic reaction:
  - swelling of your face, lips, mouth or tongue
  - trouble breathing
  - wheezing
  - severe itching
  - skin rash, hives, redness, or swelling outside of the injection site area
  - dizziness or fainting
  - fast heartbeat or pounding in your chest (tachycardia)
  - sweating
  People with DIRA may have an increased risk of allergic reactions, especially in the first several weeks.
- decreased ability of your body to fight infections (immunosuppression).It is not known if treatment with medicines that cause immunosuppression, like KINERET, affect your risk of getting cancer.
- amyloidosis. Change (rotate) injection sites within the area you chose with each dose to reduce your risk of getting injection site amyloid deposits (a hard lump under the skin). If you develop amyloid deposits, your healthcare provider should monitor for symptoms and signs of systemic amyloidosis such as protein in urine.
  o Do not use the exact same spot for each injection.
  o Do not inject into abnormal skin (e.g., skin that is bruised, red, scaly, pitted, scarred, hard, thickened, lumpy, damaged, tender or a stretch mark).
- low white blood cell count (neutropenia). KINERET may cause you to have a lower number of certain white blood cells (neutrophils). Neutrophils are important in fighting infections. You should have blood tests before starting treatment with KINERET, then monthly for 3 months. After the first 3 months you should have your blood tested every 3 months for up to 1 year.

The most common side effects of KINERET include:

- injection site skin reactions. The symptoms of injection site skin reactions may include:

- redness

- itching

- swelling

- stinging

- bruising

Most injection site reactions are mild, happen early during treatment, and last about 14 to 28 days. Injection site reactions have been observed less frequently in people with NOMID.

- rheumatoid arthritis (RA) gets worse even with treatment, if you already have RA
- headache
- nausea and vomiting
- diarrhea
- joint pain
- fever
- feeling like you have the flu
- sore throat or runny nose
- sinus infection
- pain in your stomach area

Tell your healthcare provider if you have any side effect that bothers you or that does not go away.
These are not all of the possible side effects of KINERET. For more information, ask your healthcare provider or pharmacist.
Call your doctor for medical advice about side effects. You may report side effects to FDA at 1-800-FDA-1088.

How should I store KINERET?

- Store KINERET in the refrigerator between 36°F to 46°F (2°C to 8°C).
- Do not freeze or shake KINERET.
- Keep KINERET in its original carton and away from light.

Keep KINERET and all medicines out of the reach of children.

General information about the safe and effective use of KINERET.
Medicines are sometimes prescribed for purposes other than those listed in a Patient Information Leaflet. Do not use KINERET for a condition for which it was not prescribed. Do not give KINERET to other people, even if they have the same symptoms that you have. It may harm them. You can ask your pharmacist or healthcare provider for information about KINERET that is written for health professionals.

What are the ingredients in KINERET?
Active ingredient:anakinra
Inactive ingredients:anhydrous citric acid, disodium EDTA, polysorbate 80, and sodium chloride in Water for Injection, USP.
Manufactured by:
Swedish Orphan Biovitrum AB (publ)
SE-112 76 Stockholm, Sweden
License No. 1859
© Swedish Orphan Biovitrum AB (publ). All rights reserved.
For more information, go to www.kineretrx.com or call 1-866-547-0644.

This Patient Information has been approved by the U.S. Food and Drug Administration Revised: October 2025

Instructions for Use

KINERET® (KIN-eh-ret)

(anakinra)

injection, for subcutaneous use

Read this Instructions for Use before you start using KINERET and each time you get a refill. There may be new information. This information does not take the place of talking to your healthcare provider about your medical condition or your treatment.

Supplies you will need to give your KINERET injection: See Figure A.

- 1 KINERET prefilled syringe
- 1 alcohol wipe
- 1 dry sterile gauze or tissue
- 1 puncture-resistant sharps disposal container

Figure A

Each KINERET dose comes in a prefilled glass syringe. There are 7 syringes in each new KINERET box, 1 for each day of the week. Use a new KINERET syringe each day. Use the KINERET prefilled syringe that matches the day of the week until all 7 syringes are used.

Setting up for your injection:

Step 1. Take the carton containing the prefilled syringes of KINERET out of the refrigerator. Remove the prefilled syringe from the box that matches the day of the week. Put the carton containing the remaining prefilled syringes back in the refrigerator.

Step 2.Find a clean, flat work surface, such as a table.

Step 3.Check the expiration date (EXP) on the syringe label. See Figure B.

If the expiration date has passed, do not use the syringe. Call your pharmacist or call 1-866-773-5274 for assistance.

Figure B

Step 4.Take the KINERET prefilled syringe out of the refrigerator and leave it in room temperature for 30 minutes before your injection.

Make sure the liquid medicine in the prefilled syringe is clear and colorless. It is normal to see a small amount of tiny particles that are white, or that you can see through. Do not inject the medicine if it is cloudy or discolored, or has large or colored particles. Call your healthcare provider or pharmacist if you have any questions about your KINERET prefilled syringe.

Step 5.Gather all the supplies you will need for your injection.

Step 6.Wash your hands with soap and warm water.

Preparing your correct dose of KINERET:

- Preparing a 100mg dose of KINERET:
  - Hold the syringe barrel and pull the cover straight off the needle. See Figure C. Do not touch the needle or push the plunger. Throw away the needle cover.
    Figure C
  - You may notice small air bubbles in the prefilled syringe. You do not have to remove the air bubbles before injecting. Injecting the solution with the air bubbles is harmless.
  - Carefully place the barrel of the syringe on the table until you are ready to inject. Do not let the needle touch the table. Do not recap the needle.
- How to prepare a dose of KINERET less than 100 mg:
  - Hold the syringe in 1 hand with the needle pointing straight upwards. See Figure D. Put your thumb on the plunger rod and push slowly until you see a tiny liquid drop at the tip of the needle.
    Figure D
    Turn the syringe so that the needle is now pointing downwards. Place a sterile gauze or tissue on a flat surface and hold the syringe above it with the needle pointing towards the gauze or tissue. See Figure E. Make sure the needle does not touch the gauze or tissue.
    Figure E
  - Put your thumb on the plunger rod and push slowly until you can see that the top of the plunger has reached the correct number for your KINERET dose your healthcare provider has prescribed. The liquid that was pushed out of the needle will be absorbed by the gauze or tissue. See Figure E.
  - If you are not able to select the correct dose of KINERET, throw away the syringe and use a new one.
  - Carefully place the barrel of the syringe on the table until you are ready to inject. Do not let the needle touch the table. Do not recap the needle.

Selecting and preparing the injection site:

Step 7.Choose an injection site. See Figure F.

Recommended injection sites for adults and children include:

- outer area of the upper arms
- abdomen (except the 2-inch area around the belly button)
- front of the middle thighs
- upper outer areas of the buttocks

Adult

Child

Figure F

Choose a new site each time you use KINERET. Choosing a new site may reduce your risk of getting injection site amyloid deposits (a hard lump under the skin) help avoid soreness at 1 site. Do not inject into abnormal skin (e.g., skin that is bruised, red, scaly, pitted, scarred, hard, thickened, lumpy, damaged, tender or a stretch mark). Do not inject KINERET close to a vein that you can see under the surface of your skin.

- Clean your injection site with an alcohol swab. Let the area dry completely.

Giving your injection:

Step 8.Gently pinch a fold of skin at the cleaned injection site.

Step 9.With your other hand, hold the syringe like a pencil at a 45 degree to 90 degree angle to the skin. With a quick, dart-like motion insert the needle into the skin . See Figure G.

Figure G

Step 10.After the needle is inserted into the skin, slowly push the plunger all the way down to inject KINERET. See Figure H.

Figure H

Step 11.When the syringe is empty, pull the needle out of the skin while carefully keeping the needle at the same angle as inserted. See Figure I.

Figure I

Step 12.Place a dry cotton ball or gauze pad over the injection site and press for several seconds. See Figure J. Do not use an alcohol swab as it may cause stinging. If there is a little bleeding, you may cover the injection site with a small bandage.

Figure J

Important Information about your KINERET prefilled syringe:

- Use each KINERET prefilled syringe only 1 time. Do not use a syringe more than 1 time. Do not recap a needle.
- You may not have to use all of the liquid medicine in the prefilled syringe. Your healthcare provider will show you how to find the correct dose of KINERET for you or your child.
- If you notice that some medicine is left in the prefilled syringe, do not inject again with the same prefilled syringe.
- If you drop a prefilled syringe, do not use it.The glass syringe may be broken, or the needle may be bent or dirty. Throw away the prefilled syringe and replace it with a new one. Take a new prefilled syringe from what would be the last day of the week in your current box. For example, if you start on Wednesday, the last day of the week in your series is Tuesday. After using all the remaining prefilled syringes in your current box, start your next box of KINERET prefilled syringes.

Disposal of your KINERET syringes:

- Put your used syringes in a FDA-cleared sharps disposal container right away after use. Do not throw away (dispose of) loose syringes in your household trash.
- If you do not have a FDA-cleared sharps disposal container, you may use a household container that is:
  - made of a heavy-duty plastic
  - can be closed with a tight-fitting, puncture-resistant lid, without sharps being able to come out
  - upright and stable during use
  - leak-resistant
  - properly labeled to warn of hazardous waste inside the container
- When your sharps disposal container is almost full, you will need to follow your community guidelines for the right way to dispose of your sharps disposal container. There may be state or local laws about how you should throw away used needles and syringes. For more information about safe sharps disposal, and for specific information about sharps disposal in the state that you live in, go to the FDA's website at: http://www.fda.gov/safesharpsdisposal.
- Do not dispose of your used sharps disposal container in your household trash unless your community guidelines permit this. Do not recycle your used sharps disposal container.
- Throw away the wet gauze or tissue with your syringe and clean the table surface with a fresh swab.

This Patient Information and Instructions for Use has been approved by the U.S. Food and Drug Administration.

sobi
SWEDISH ORPHAN BIOVITRUM

Manufactured by:
Swedish Orphan Biovitrum AB (publ)
SE-112 76 Stockholm, Sweden
License No. 1859

© Swedish Orphan Biovitrum AB (publ). All rights reserved. Revised Date: 10/2025

Principal Display Panel - Carton Label

4 x 7 Syringe Dispensing Packs (28 x 100 mg/0.67 mL Prefilled Glass Syringes) NDC 66658-234-28

sobi

Kineret®
(anakinra)

Injecton

100 mg/0.67 mL

Single Use: Discard Any Unused Portion

Subcutaneous Use Only

Graduated Prefilled Glass Syringes with 29 Gauge Needles

Sterile Solution - No Preservative

Manufactured by Swedish Orphan Biovitrum AB (publ)

SE-112 76 Stockholm, Sweden

License # 1859 RxOnly

Principal Display Panel - Carton Label

(Seven x 100 mg/0.67 mL Prefilled Glass Syringes) NDC 66658-234-07

sobi

Kineret®
(anakinra)

Injecton

100 mg/0.67 mL

Single Use: Discard Any Unused Portion

Subcutaneous Use Only

Graduated Prefilled Glass Syringes with 29 Gauge Needles

Sterile Solution - No Preservative

Refrigerate at 2 °to 8 °C (36 °to 46 °F). Do Not Freeze or Shake.

Protect from Light.

Rx Only

Manufactured by Swedish Orphan Biovitrum AB (publ)

SE-112 76 Stockholm, Sweden

License # 1859